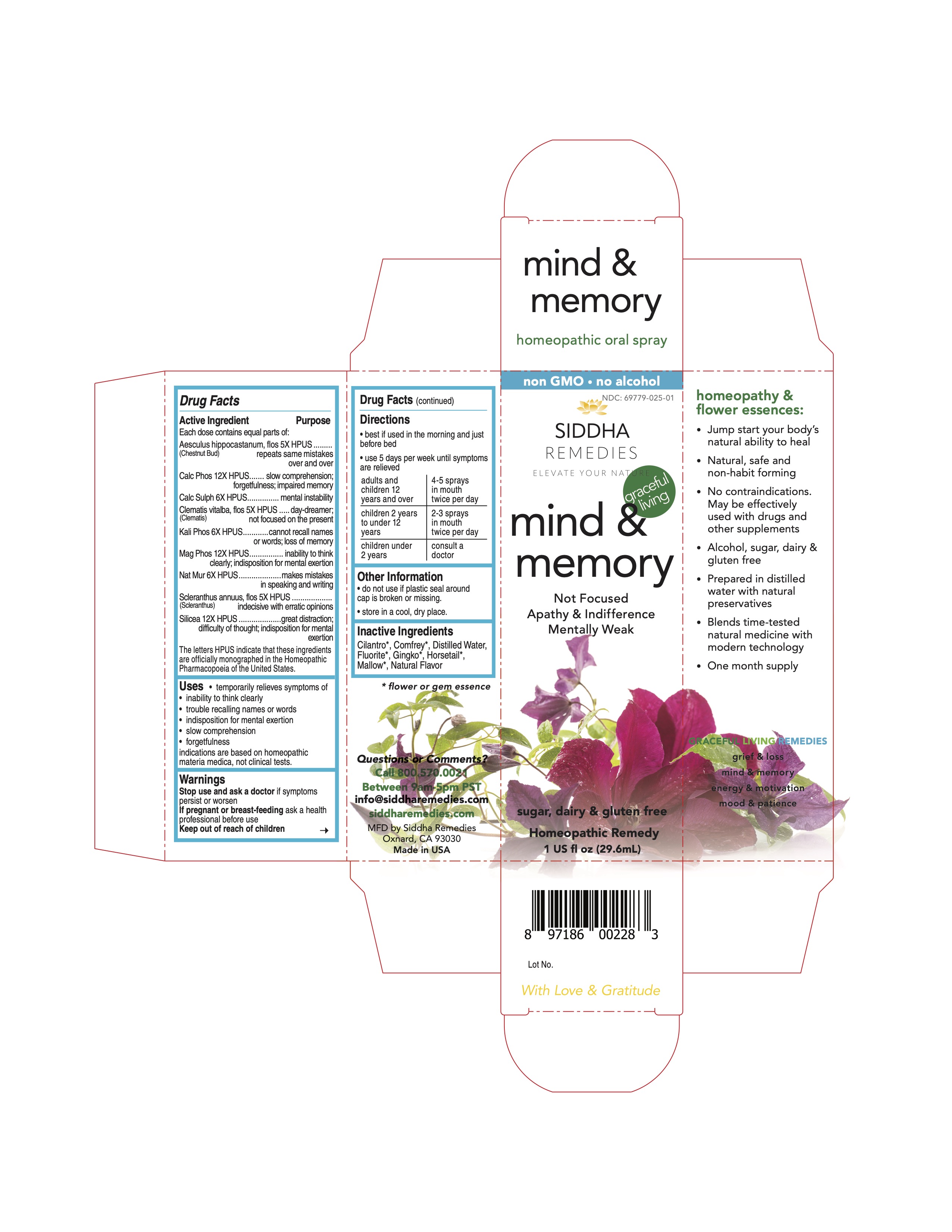 DRUG LABEL: mind and memory
NDC: 69779-025 | Form: SPRAY
Manufacturer: Siddha Flower Essences LLC
Category: homeopathic | Type: HUMAN OTC DRUG LABEL
Date: 20251231

ACTIVE INGREDIENTS: HORSE CHESTNUT 5 [hp_X]/29.6 mL; TRIBASIC CALCIUM PHOSPHATE 12 [hp_X]/29.6 mL; CALCIUM SULFATE ANHYDROUS 6 [hp_X]/29.6 mL; CLEMATIS VITALBA FLOWER 5 [hp_X]/29.6 mL; DIBASIC POTASSIUM PHOSPHATE 6 [hp_X]/29.6 mL; MAGNESIUM PHOSPHATE, DIBASIC TRIHYDRATE 12 [hp_X]/29.6 mL; SODIUM CHLORIDE 6 [hp_X]/29.6 mL; SCLERANTHUS ANNUUS FLOWERING TOP 5 [hp_X]/29.6 mL; SILICON DIOXIDE 12 [hp_X]/29.6 mL
INACTIVE INGREDIENTS: CILANTRO; SYMPHYTUM UPLANDICUM LEAF; CALCIUM FLUORIDE; GINKGO; EQUISETUM ARVENSE TOP; MALVA SYLVESTRIS FLOWERING TOP; WATER

Active Ingredient

Each dose contains equal parts of:

Aesculus hippocastanum, flos (Chestnut Bud) 5X HPUS

Calc Phos 12X HPUS

Calc Sulph 6X HPUS

Clematis vitalba, flos (Clematis) 5X HPUS

Kali Phos 6X HPUS

Mag Phos 12X HPUS

Nat Mur 6X HPUS

Scleranthus annuus, flos (Scleranthus) 5X HPUS

Silicea 12X HPUS

Purpose

Each dose contains equal parts of:

Aesculus hippocastanum, flos (Chestnut Bud) 5X HPUS......repeats same mistakes over and over

Calc Phos 12X HPUS......................................................slow comprehension; forgetfulness; impaired memory

Calc Sulph 6X HPUS......................................................mental instability

Clematis vitalba, flos (Clematis) 5X HPUS.........................day-dreamer; not focused on the present

Kali Phos 6X HPUS........................................................cannot recall names or words; loss of memory

Mag Phos 12X HPUS......................................................inability to think clearly; indisposition for mental exertion

Nat Mur 6X HPUS..........................................................makes mistakes in speaking and writing

Scleranthus annuus, flos (Scleranthus) 5X HPUS...............indecisive with erratic opinions

Silicea 12X HPUS..........................................................great distraction; difficulty of thought; indisposition for mental exertion

Uses

temporarily relieves symptoms of

- inability to think clearly
- trouble recalling names or words
- indisposition for mental exertion
- slow comprehension
- forgetfulness

indications are based on homeopathic materia medica, not clinical tests.

Uses

Stop use and ask a doctor if symptoms persist or worsen

PREGNANCY OR BREAST FEEDING

If pregnant or breast-feeding ask a health professional before use

Keep out of reach of children

Directions

- best if used in the morning and just before bed
- use 5 days per week until symptoms are relieved

adults and children 12 years and over | 4-5 sprays in mouth twice per day
children 2 years to under 12 years | 2-3 sprays in mouth twice per day
children under 2 years | consult a doctor

Other Information

- do not use if plastic seal around cap is broken or missing.
- store in a cool, dry place.

Inactive Ingredients

Cilantro*, Comfrey*, Fluorite*, Ginkgo*, Horsetail*, Mallow*, Natural Flavor, Neon*, Purified Water

*flower or gem essence

Questions or Comments?
Call 800.570.0021
Between 9am-5pm PST
info@siddhaflowers.com
siddhaflowers.com
MFD by Siddha Flower Essences
Oxnard, CA 93030
Made in USA

Side Panel

homeopathy and flower essences:

- Jump start your body's natural ability to heal
- Natural, safe and non-habit forming
- No contraindications. May be effectively used with drugs and other supplements
- Alcohol, sugar, dairy and gluten free
- Prepared in purified water with natural preservatives
- Blends time-tested natural medicine with modern technology
- One month supply

GRACEFUL AGING REMEDIES

grief & loss

mind & memory

energy & motivation

mood & patience

Principal Display Panel

non GMO - no alcohol
siddha cell salts + flower essences
mind & memory
Not Focused

Apathy & Indifference

Mentally Weak
sugar, dairy & gluten free
Homeopathic Remedy
1 US fl oz (29.6mL)